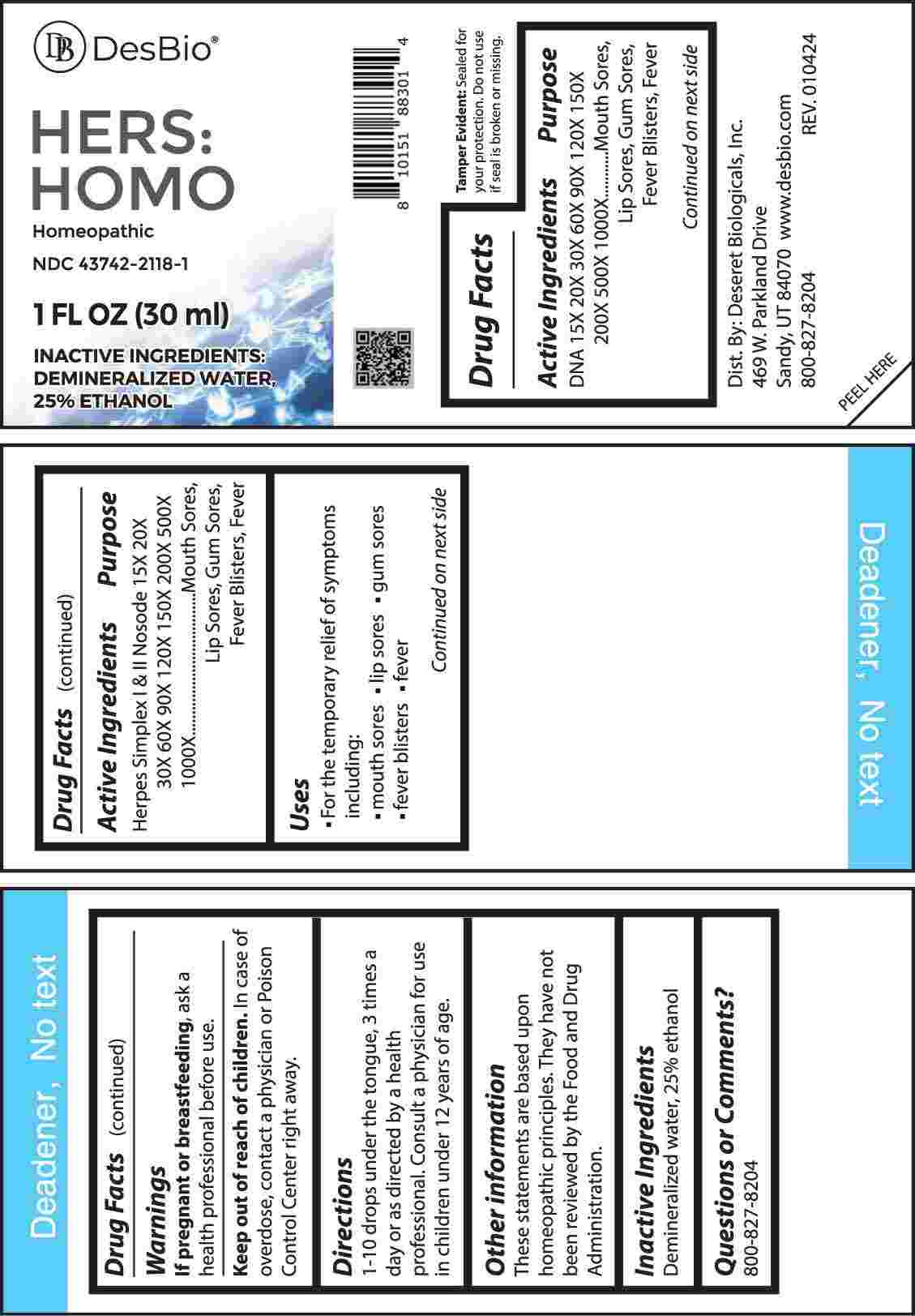 DRUG LABEL: Hers Homo
NDC: 43742-2118 | Form: LIQUID
Manufacturer: Deseret Biologicals, Inc.
Category: homeopathic | Type: HUMAN OTC DRUG LABEL
Date: 20240418

ACTIVE INGREDIENTS: HERRING SPERM DNA 15 [hp_X]/1 mL; HUMAN HERPESVIRUS 1 15 [hp_X]/1 mL; HUMAN HERPESVIRUS 2 15 [hp_X]/1 mL
INACTIVE INGREDIENTS: WATER; ALCOHOL

DRUG FACTS:

ACTIVE INGREDIENTS:

DNA 15X, 20X, 30X, 60X, 90X, 120X, 150X, 200X, 500X, 1000X, Herpes Simplex I & II Nosode 15X, 20X, 30X, 60X, 90X, 120X, 150X, 200X, 500X, 1000X.

PURPOSE:

DNA - Mouth Sores, Lip Sores, Gum Sores, Fever Blisters, Fever, Herpes Simplex I & II Nosode - Mouth Sores, Lip Sores, Gum Sores, Fever Blisters, Fever

USES:

• For the temporary relief of symptoms including:

• mouth sores • lip sores • gums sores

• fever blisters • fever

These statements are based upon homeopathic principles. They have not been reviewed by the Food and Drug Administration.

WARNINGS:

If pregnant or breast-feeding, ask a health professional before use.

Keep out of reach of children. In case of overdose, contact a physician or Poison Control Center right away.

Tamper Evident: Sealed for your protection. Do not use if seal is broken or missing.

KEEP OUT OF REACH OF CHILDREN:

In case of overdose, contact a physician or Poison Control Center right away.

DIRECTIONS:

1-10 drops under the tongue, 3 times a day or as directed by a health professional. Consult a physician for use in children under 12 years of age.

INACTIVE INGREDIENTS:

Demineralized water, 25% ethanol

QUESTIONS:

Dist. By: Deseret Biologicals, Inc.
469 W. Parkland Drive
Sandy, UT 84070

www.desbio.com

800-827-8204

PACKAGE LABEL DISPLAY:

DesBio

HERS:HOMO

Homeopathic

NDC 43742-2118-1

1 FL OZ (30 ml)